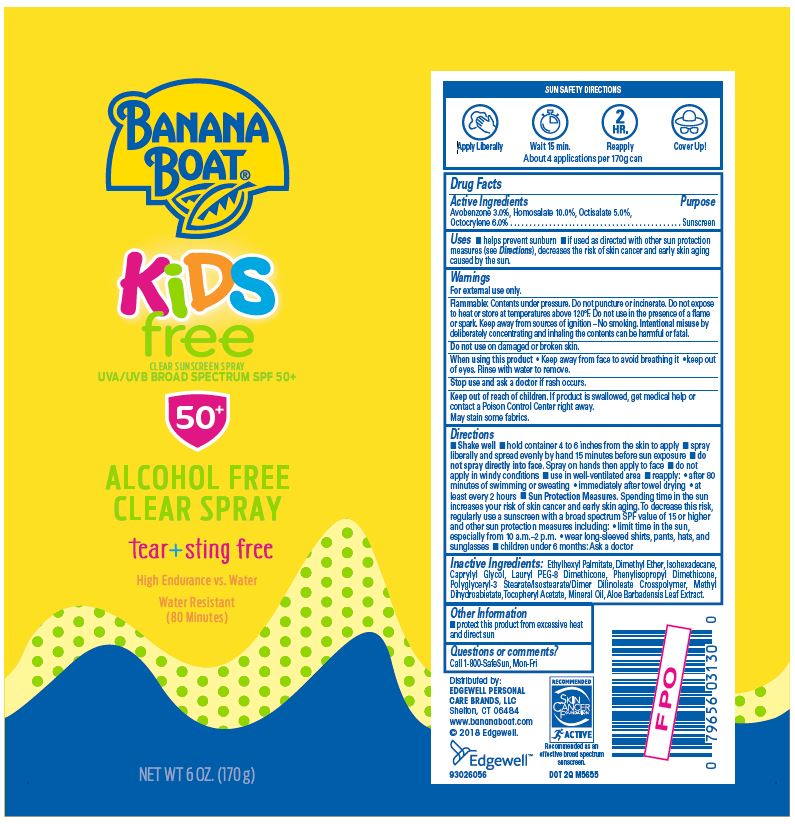 DRUG LABEL: BANANA BOAT KIDS FREE 50
NDC: 63354-115 | Form: SPRAY
Manufacturer: Edgewell Personal Care Brands, LLC
Category: otc | Type: HUMAN OTC DRUG LABEL
Date: 20231122

ACTIVE INGREDIENTS: Octisalate 5 g/100 g; Octocrylene 6 g/100 g; Avobenzone 3 g/100 g; Homosalate 10 g/100 g
INACTIVE INGREDIENTS: Aloe Vera Leaf; Dimethyl Ether; Ethylhexyl Palmitate; Isohexadecane; Caprylyl Glycol; Hydrogenated Methyl Abietate; Mineral Oil

Active Ingredients

Avobenzone 3.0%, Homosalate 10.0%, Octisalate 5.0%, Octocrylene 6.0%

Purpose

Sunscreen

Uses

• helps prevent sunburn • If used as directed with other sun protectiion measures (see Directions), decreases the risk of skin cancer and early skin aging caused by the sun.

Warnings

For external use only.

Flammable: Contents under pressure. Do not puncture or incinerate. Do not expose to heat or store at temperatures above 120°F. Do not use in the presence of a flame or spark. Keep away from sources of ignition – No smoking. Intentional misuse by deliberately concentrating and inhaling the contents can be harmful or fatal.

May stain some fabrics.

Do not use

on damaged or broken skin.

When using this product

• keep away from face to avoid beathing it • keep out of eyes. Rinse with water to remove.

Stop use and ask a doctor

if rash occurs.

Keep out of reach of children.

If product is swallowed, get medical help or contact a Poison Control Center right away.

Directions

• Shake well • hold container 4 to 6 inches from the skin to apply • spray liberally and evenly by hand 15 minutes before sun exposure • do not spray directly into face. Spray on hands then apply to face • do not apply in windy conditions • use in well-ventilated area. • reapply • after 80 minues of swimming or sweating • immediately after towel drying • at least every 2 hours • Sun Protection Measures. Spending time in the sun increases your risk of skin cancer and early skin aging. To decrease this risk, regularly use a sunscreen with a broad spectrum SPF of 15 or higher and other sun protection measures including: • limit time in the sun, especially from 10 a.m.-2 p.m. • wear long-sleeve shirts, pants, hats, and sunglasses • children under 6 months: Ask a doctor.

Inactive Ingrdients

Ethylhexyl Palmitate, Dimethyl Ether, Isohexadecane, Caprylyl Glycol, Lauryl PEG-8 Dimethicone, Phenylisopropyl Dimethicone, Polyglyceryl-3 Stearate/Isostearate/Dimer Dilinoleate Crosspolymer, Methyl Dihydroabietate, Tocopheryl Acetate, Mineral Oil, Aloe Barbadensis Leaf Extract.

Other Information

protect this product from excessive heat and direct sun

Questions or comments?

• protect this product from excessive heat and direct sun

Principal Display Panel

BANANA
BOAT®
KiDS
free
CLEAR SUNSCREEN SPRAY
UVA/UVB BROAD SPECTRUM SPF 50+
50+
ALCOHOL FREE
CLEAR SPRAY
tear+sting free
High Endurance vs. Water
Water Resistant
(80 Minutes)
NET WT 6 OZ. (170 g)